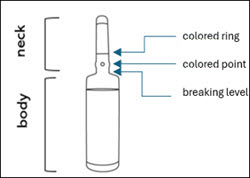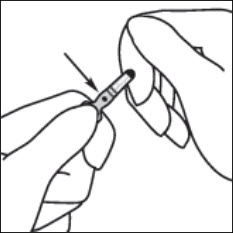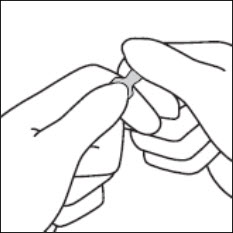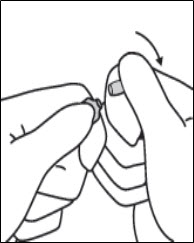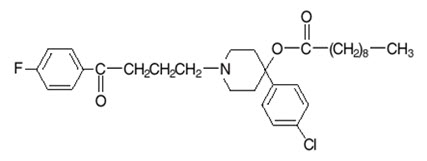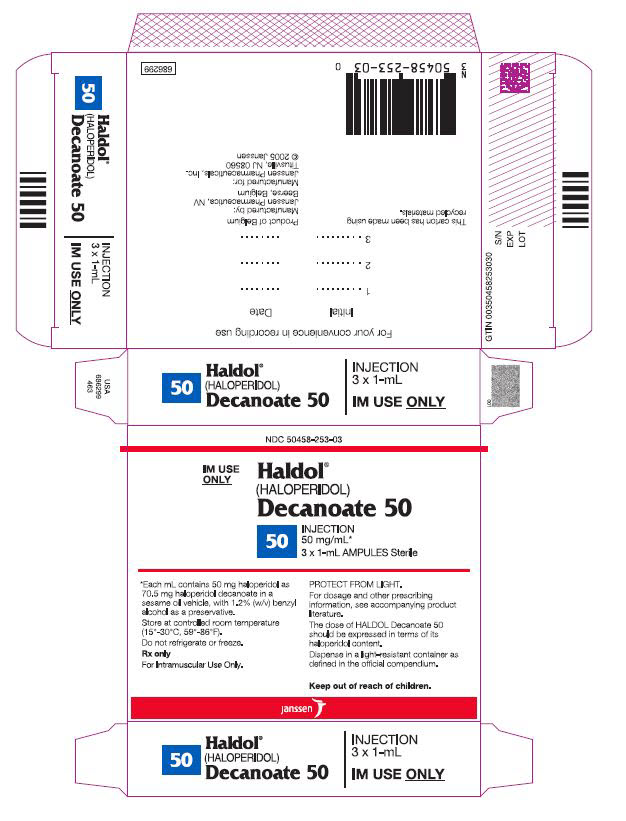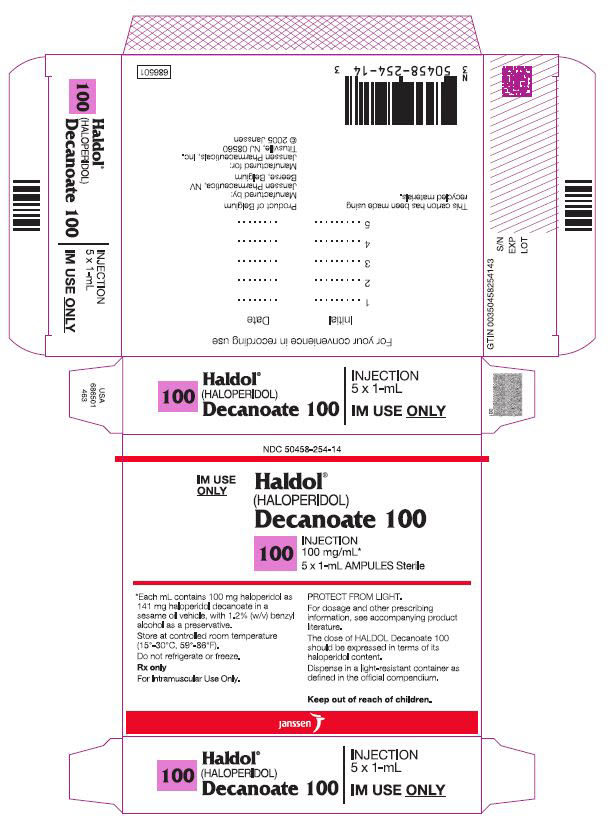 DRUG LABEL: Haldol Decanoate
NDC: 50458-253 | Form: INJECTION
Manufacturer: Janssen Pharmaceuticals, Inc.
Category: prescription | Type: HUMAN PRESCRIPTION DRUG LABEL
Date: 20251111

ACTIVE INGREDIENTS: HALOPERIDOL DECANOATE 50 mg/1 mL
INACTIVE INGREDIENTS: BENZYL ALCOHOL; SESAME OIL

HIGHLIGHTS OF PRESCRIBING INFORMATION

These highlights do not include all the information needed to use HALDOL DECANOATE safely and effectively. See full prescribing information for HALDOL DECANOATE.
HALDOL DECANOATE (haloperidol decanoate injection), for intramuscular use
Initial U.S. Approval: 1986

WARNING: INCREASED MORTALITY IN ELDERLY PATIENTS WITH DEMENTIA-RELATED PSYCHOSIS

See full prescribing information for complete boxed warning.

Elderly patients with dementia-related psychosis treated with antipsychotic drugs are at an increased risk of death. HALDOL DECANOATE is not approved for the treatment of patients with dementia-related psychosis (5.1).

1 INDICATIONS AND USAGE

HALDOL DECANOATE is a typical antipsychotic indicated for the treatment of schizophrenia in adults who were previously taking a stable dosage of an immediate-release oral haloperidol product (1).

2 DOSAGE AND ADMINISTRATION

- Administer HALDOL DECANOATE by deep intramuscular injection every 4 weeks by a healthcare provider. Do not administer intravenously(2.1).
- For the recommended dosage, including the first recommended dose and the maintenance dosage, see the Dosage and Administration section (2.1).
- If schizophrenia symptoms worsen during dosage modification of HALDOL DECANOATE, consider administering an immediate-release oral haloperidol product in addition to HALDOL DECANOATE therapy (2.2).

3 DOSAGE FORMS AND STRENGTHS

Injection:

- Haloperidol 50 mg/mL (present as haloperidol decanoate) in single-dose ampules (3).
- Haloperidol 100 mg/mL (present as haloperidol decanoate) in single-dose ampules (3).

4 CONTRAINDICATIONS

- Severe toxic central nervous system depression or comatose states from any cause (4).
- Known hypersensitivity to haloperidol or any components of HALDOL DECANOATE (4).
- Parkinson's disease (4, 5.7, 6.1).
- Dementia with Lewy bodies (4, 5.7).

5 WARNINGS AND PRECAUTIONS

- Sudden Death, Torsades de Pointes (TdP), and QTc Interval Prolongation:Avoid use of HALDOL DECANOATE in patients who are at risk of developing TdP. Avoid concomitant use of HALDOL DECANOATE with drugs that may increase risk of QTc interval prolongation or increase haloperidol exposure. Obtain ECG and serum electrolytes at baseline and during treatment as clinically indicated (5.2).
- Tachycardia and Hypotension:Monitor orthostatic vital signs (5.3).
- Cerebrovascular Adverse Reactions Including Stroke in Elderly Patients with Dementia-Related Psychosis:Use with caution in patients with schizophrenia who have risk factors for cerebrovascular adverse reactions (5.4).
- Tardive Dyskinesia:Discontinue treatment if clinically appropriate (5.5).
- Neuroleptic Malignant Syndrome (NMS):Immediately discontinue and monitor closely (5.6).
- Seizures:HALDOL DECANOATE is generally not recommended in patients receiving antiseizure drugs or who have a history of seizures or EEG abnormalities. If clinically, indicated, maintain patients taking HALDOL DECANOATE on adequate antiseizure therapy (5.8).
- Potential for Cognitive and Motor Impairment:Advise patients to not drive a motor vehicle or operate hazardous machinery until they are reasonably certain HALDOL DECANOATE does not impair their cognitive and motor functions (5.11).
- Risk of Encephalopathic Syndrome with Concomitant Use of Lithium:Monitor closely for early signs of neurological toxicity and discontinue HALDOL DECANOATE if such signs appear (5.12).
- Leukopenia, Neutropenia, and Agranulocytosis:Perform complete blood counts (CBC) in patients with pre-existing low white blood cell count (WBC) or history of leukopenia or neutropenia. Consider discontinuing HALDOL DECANOATE if clinically significant decline in WBC occurs in absence of other causative factors. Discontinue HALDOL DECANOATE in patients with clinically significant neutropenia or an absolute neutrophile count of <1,000/mm^3(5.13).
- Hyperprolactinemia:Elevated prolactin levels may occur during acute and chronic use (5.14).

6 ADVERSE REACTIONS

The most common adverse reactions (incidence ≥5%) were oculogyric crisis and parkinsonism (6.1).

To report SUSPECTED ADVERSE REACTIONS, contact Janssen Pharmaceuticals, Inc. at 1-800-JANSSEN (1-800-526-7736) or FDA at 1-800-FDA-1088 or www.fda.gov/medwatch.

7 DRUG INTERACTIONS

- Drugs that Prolong QTc Interval:Avoid concomitant use with HALDOL DECANOATE (7.1).
- See full prescribing information for additional clinically significant drug interactions with HALDOL DECANOATE (7.2).

8 USE IN SPECIFIC POPULATIONS

- Pregnancy:Neonates exposed to HALDOL DECANOATE during the third trimester of pregnancy may develop extrapyramidal and/or withdrawal symptoms (agitation, hypertonia, hypotonia, tremor, somnolence, respiratory distress, and decreased feeding) (8.1).
- Lactation:Monitor breastfed infants for excessive sedation, irritability, poor feeding, abnormal muscle movements, and tremors (8.2).

FULL PRESCRIBING INFORMATION

WARNING: INCREASED MORTALITY IN ELDERLY PATIENTS WITH DEMENTIA-RELATED PSYCHOSIS

Elderly patients with dementia-related psychosis treated with antipsychotic drugs are at an increased risk of death. HALDOL DECANOATE is not approved for the treatment of patients with dementia-related psychosis [see Warnings and Precautions (5.1)] .

1 INDICATIONS AND USAGE

HALDOL DECANOATE is indicated for the treatment of schizophrenia in adults who were previously taking a stable dosage of an immediate-release oral haloperidol product.

2 DOSAGE AND ADMINISTRATION

2.1 Recommended Dosage and Administration

Administer HALDOL DECANOATE by deep intramuscular injection every 4 weeks by a health care professional. Do not administer HALDOL DECANOATE intravenously.

When injecting HALDOL DECANOATE, use a 21-gauge needle. The maximum volume per injection site is 3 mL.

Table 1 below describes the recommended dosage for HALDOL DECANOATE. The maximum recommended initial dose is 100 mg. If the calculated first recommended dose of HALDOL DECANOATE is greater than 100 mg, then administer two deep intramuscular injections as follows:

- 100 mg on the first day
- Remainder of the amount 3 to 7 days later.

Table 1: HALDOL DECANOATE Recommended Dosage
Population | First Recommended Dose | Maintenance Dosage [Clinical experience with HALDOL DECANOATE at a dosage greater than 450 mg every 4 weeks has been limited.]
Adult patients less than 65 years old stabilized on ≤ 10 mg of daily immediate-release oral haloperidol with normal hepatic function. | 10–15 times previous daily dose of immediate-release oral haloperidol. | 10–15 times previous daily dose of immediate-release oral haloperidol administered every 4 weeks. The dosage may be increased by increments of 50 mg or less every 4 weeks until an optimal therapeutic effect is obtained. The typical effective dosage range is between 50 and 200 mg every 4 weeks.
Adult patients less than 65 years old stabilized on ≤ 10 mg of daily immediate-release oral haloperidol with hepatic impairment OR Adult patients 65 years and older | 10–15 times previous daily dose of immediate-release oral haloperidol. Consider starting at the low end of the dosing range [see Use in Specific Populations (8.5, 8.6)and Clinical Pharmacology (12.3)]. | 10–15 times previous daily dose of immediate-release oral haloperidol administered every 4 weeks. The dosage may be increased by increments of 50 mg or less every 4 weeks until an optimal therapeutic effect is obtained. The typical effective dosage range is between 50 and 200 mg every 4 weeks.
Adult patients less than 65 years old stabilized on >10 mg of daily immediate-release oral haloperidol | 10–20 times previous daily dose of immediate-release oral haloperidol | 10–15 times previous daily dose of immediate-release oral haloperidol administered every 4 weeks. The dosage may be increased by increments of 50 mg or less every 4 weeks until an optimal therapeutic effect is obtained.

2.2 Recommended Supplemental Immediate-release Oral Haloperidol Therapy

If schizophrenia symptoms worsen during dosage modification of HALDOL DECANOATE, consider administering an immediate-release oral haloperidol product in addition to HALDOL DECANOATE therapy.

2.3 Preparation Instructions

Visually inspect HALDOL DECANOATE for particulate matter and discoloration prior to administration. Do not use if the solution has debris or is not clear or not yellow to light amber in color.

Instructions for breaking the ampule are as follows:

Step 1 |  | Figure A
1. | Because some fluid may be in the top of the ampule, lightly tap the top of the ampule with your finger until all fluid moves to the bottom portion of the ampule before breaking the ampule. The colored ring and colored point of the ampule aid the placement of fingers while breaking the ampule (see Figure A).
Step 2 |  | Figure B
2. | Hold the ampule between the thumb and index finger with the colored point facing you (see Figure B).
Step 3 |  | Figure C
3. | Position the index finger of the other hand to support the neck of the ampule. Position the thumb of the same hand so that it covers the colored point and is parallel to the colored ring (see Figure C).
Step 4 |  | Figure D
4. | With the thumb on the colored point and index fingers close together, apply firm pressure on the colored point and push away from your body, in the direction of the arrow, to snap the ampule open at the breaking level (see Figure D).

3 DOSAGE FORMS AND STRENGTHS

Injection:

- Haloperidol 50 mg/mL (present as haloperidol decanoate) is a clear, yellow to light amber viscous liquid, free from visible foreign material, in a single-dose ampule
- Haloperidol 100 mg/mL (present as haloperidol decanoate) is a clear, yellow to light amber viscous liquid, free from visible foreign material, in a single-dose ampule

4 CONTRAINDICATIONS

HALDOL DECANOATE is contraindicated in patients with:

- Severe toxic central nervous system depression or comatose states from any cause.
- Known hypersensitivity to haloperidol or any components of HALDOL DECANOATE. Hypersensitivity reactions, including anaphylactic reactions and angioedema, have been reported in patients treated with haloperidol [see Warnings and Precautions (5.9)and Adverse Reactions (6.2)] .
- Parkinson's disease [see Warnings and Precautions (5.7)].
- Dementia with Lewy bodies [see Warnings and Precautions (5.7)] .

5 WARNINGS AND PRECAUTIONS

5.1 Increased Mortality in Elderly Patients with Dementia-Related Psychosis

Elderly patients with dementia-related psychosis treated with antipsychotic drugs are at an increased risk of death. In an analysis of 17 placebo-controlled trials (modal duration of 10 weeks), largely in patients taking atypical antipsychotic drugs, the risk of death in antipsychotic drug-treated patients was 1.6 to 1.7 times the risk of death in placebo-treated patients. Over the course of a typical 10-week controlled trial, the incidence of death in antipsychotic drug-treated patients was about 4.5%, compared to an incidence of about 2.6% in placebo-treated patients. Although the causes of death were varied, most of the deaths appeared to be either cardiovascular (e.g., heart failure, sudden death) or infectious (e.g., pneumonia) in nature.

HALDOL DECANOATE is not approved for the treatment of patients with dementia-related psychosis [see Indications and Usage (1)] .

5.2 Sudden Death, Torsades de Pointes, and QTc Interval Prolongation

Cases of sudden death, torsades de pointes (TdP) and QTc interval prolongation have been reported in haloperidol-treated patients [see Adverse Reactions (6.1, 6.2)] . Cases have been reported even in the absence of predisposing factors. Higher than recommended haloperidol dosages were associated with a higher risk of TdP and QTc interval prolongation.

Avoid use of HALDOL DECANOATE in patients who are at significant risk of developing TdP including those with congenital long QT syndrome, uncontrolled or significant cardiac disease, recent myocardial infarction, ischemic cardiomyopathy, unstable angina, bradyarrhythmias, uncontrolled hypertension, high degree atrioventricular block, severe aortic stenosis, or uncontrolled hypothyroidism. Avoid the concomitant use of HALDOL DECANOATE with drugs that may increase the risk of the QTc interval prolongation or increase haloperidol exposure. Assess the QTc interval via an ECG at baseline, and during treatment as clinically indicated. Obtain serum electrolytes (including potassium, calcium, phosphorus, and magnesium) at baseline and during treatment as clinically indicated, and correct electrolyte abnormalities.

5.3 Tachycardia and Hypotension

Tachycardia and hypotension (including orthostatic hypotension) have been reported in patients treated with haloperidol [see Adverse Reactions (6.1)] . Orthostatic vital signs should be monitored in patients who are at risk for hypotension (e.g., geriatric patients, patients with dehydration, hypovolemia, and concomitantly treated with antihypertensive medications), patients with known cardiovascular disease (history of myocardial infarction, ischemic heart disease, heart failure, or conduction abnormalities), and patients with cerebrovascular disease.

Should hypotension occur and a vasopressor be required, epinephrine must not be used since HALDOL DECANOATE may block its vasopressor activity, and paradoxically lower blood pressure. Instead, metaraminol, phenylephrine or norepinephrine should be used.

5.4 Cerebrovascular Adverse Reactions Including Stroke in Elderly Patients with Dementia-Related Psychosis

In placebo-controlled trials, elderly patients with dementia-related psychosis treated with antipsychotics had an increased risk of cerebrovascular adverse reactions (e.g., stroke, transient ischemic attack) including fatalities, compared to those treated with placebo. The mechanism for this increased risk is not known.

HALDOL DECANOATE is not approved for the treatment of patients with dementia-related psychosis. HALDOL DECANOATE should be used with caution in patients with schizophrenia who have risk factors for cerebrovascular adverse reactions.

5.5 Tardive Dyskinesia

Tardive dyskinesia (TD) may develop in patients treated with antipsychotic drugs, including HALDOL DECANOATE [see Adverse Reactions (6.1)] . TD can develop after a relatively brief treatment period at low dosages and may also occur after discontinuation of treatment. If antipsychotic treatment is discontinued, TD may partially or completely remit. Antipsychotic treatment, however, may suppress or partially suppress the signs and symptoms of TD and may mask the underlying process. The effect that symptomatic suppression has upon the long-term course of TD is unknown.

The TD risk in patients treated with antipsychotic drugs appears to be highest among the elderly, especially elderly women, but it is not possible to predict, which patients are likely to develop TD. The TD risk and the likelihood that TD will become irreversible increase with the duration of antipsychotic drug treatment and the cumulative dosage.

In patients who require chronic antipsychotic treatment, use the lowest dosage and the shortest duration of treatment that produces a satisfactory clinical response. Periodically reassess the need for continued treatment. If signs and symptoms of TD appear in HALDOL DECANOATE-treated patients, consider drug discontinuation. However, some patients may require HALDOL DECANOATE treatment despite the presence of TD.

5.6 Neuroleptic Malignant Syndrome

Neuroleptic Malignant Syndrome (NMS), a potentially fatal symptom complex, has been reported in association with the use of antipsychotic drugs [see Adverse Reactions (6.1)] . Clinical manifestations of NMS are hyperpyrexia, muscle rigidity, delirium, and autonomic instability, and additional signs may include elevated creatine phosphokinase, myoglobinuria (rhabdomyolysis), and acute renal failure.

If NMS is suspected, immediately discontinue HALDOL DECANOATE and provide intensive symptomatic treatment and monitoring.

5.7 Neurological Adverse Reactions in Patients with Parkinson's Disease or Dementia with Lewy Bodies

Patients with Parkinson's disease or Dementia with Lewy bodies may experience increased sensitivity to haloperidol. Manifestations of this increased sensitivity include severe extrapyramidal symptoms (e.g., tremor, rigidity, bradykinesia), confusion, sedation, and falls. HALDOL DECANOATE is contraindicated in patients with Dementia with Lewy bodies and in patients with Parkinson's disease.

5.8 Seizures

HALDOL DECANOATE may lower the seizure threshold. HALDOL DECANOATE is generally not recommended in patients receiving antiseizure drugs or have a history of seizures or EEG abnormalities. If clinically indicated, maintain patients taking HALDOL DECANOATE on adequate antiseizure therapy.

5.9 Hypersensitivity Reactions

There have been postmarketing reports of hypersensitivity reactions with haloperidol including anaphylactic reaction, angioedema, dermatitis exfoliative, hypersensitivity vasculitis, rash, urticaria, face edema, laryngeal edema, bronchospasm, and laryngospasm [see Adverse Reactions (6.2)] .

HALDOL DECANOATE is contraindicated in patients with known hypersensitivity to haloperidol or any components of HALDOL DECANOATE.

5.10 Falls

Antipsychotics, including HALDOL DECANOATE, may cause somnolence, orthostatic hypotension, motor instability and sensory abnormality, which may lead to falls and, consequently, fractures and other injuries.

If patients have a condition (or take concomitant drugs) that could exacerbate these effects, complete fall risk assessments when initiating HALDOL DECANOATE treatment and periodically during long-term treatment.

5.11 Potential for Cognitive and Motor Impairment

HALDOL DECANOATE may impair judgement, thinking, or motor skills. Inform patients of the risk and advise them to not drive a motor vehicle or operate hazardous machinery until they are reasonably certain that treatment with HALDOL DECANOATE does not impair their cognitive and motor functions.

5.12 Risk of Encephalopathic Syndrome with Concomitant Use of Lithium

An encephalopathic syndrome, characterized by weakness, lethargy, fever, tremulousness, confusion, extrapyramidal symptoms, leukocytosis, and elevated serum enzymes (AST, ALT, GGT, alkaline phosphatase, CK, and LDH), BUN, and fasting blood sugar, followed by irreversible brain damage has occurred in a few patients treated with concomitant haloperidol and lithium.

Monitor patients who concomitantly use HALDOL DECANOATE and lithium closely for early signs of neurological toxicity, and discontinue HALDOL DECANOATE or both HALDOL DECANOATE and lithium promptly if such signs appear.

5.13 Leukopenia, Neutropenia, and Agranulocytosis

Leukopenia, neutropenia and agranulocytosis (including fatal cases) have been reported during treatment with antipsychotic drugs, including HALDOL DECANOATE [see Adverse Reactions (6.2)] .

Possible risk factors for antipsychotic drug-associated leukopenia and neutropenia include pre-existing low WBC and history of drug-induced leukopenia and neutropenia.

Perform frequent complete blood count (CBC) monitoring during the first few months of HALDOL DECANOATE therapy in patients with a history of a clinically significant low WBC, drug-induced leukopenia or neutropenia. Consider discontinuing HALDOL DECANOATE in patients who have a clinically significant decline in their WBC in the absence of other causative factors. Discontinue HALDOL DECANOATE in patients with clinically significant neutropenia or an absolute neutrophil count of <1,000/mm^3and monitor closely until the neutropenia resolves.

5.14 Hyperprolactinemia

Antipsychotic drugs elevate prolactin levels during acute and chronic use and may result in galactorrhea, amenorrhea, gynecomastia, and impotence which have been reported with antipsychotic drugs [see Adverse Reactions (6.1, 6.2)and Use in Specific Populations (8.3)] .

Published epidemiologic studies have shown inconsistent results regarding the potential association between hyperprolactinemia and breast cancer [see Nonclinical Toxicology (13.1)] .

5.15 Risk of Severe Neurotoxicity in Patients with Thyrotoxicosis

Severe neurotoxicity (rigidity, inability to walk or talk) may occur in patients with thyrotoxicosis who are also receiving antipsychotic drugs, including HALDOL DECANOATE.

6 ADVERSE REACTIONS

The following adverse reactions are discussed in more detail in other sections of the labeling:

- Sudden Death, Torsades de Pointes, and QTc Interval Prolongation [see Warnings and Precautions (5.2)]
- Tachycardia and Hypotension [see Warnings and Precautions (5.3)]
- Tardive Dyskinesia [see Warnings and Precautions (5.5)]
- Neuroleptic Malignant Syndrome [see Warnings and Precautions (5.6)]
- Seizures [see Warnings and Precautions (5.8)]
- Hypersensitivity Reactions [see Warnings and Precautions (5.9)]
- Leukopenia, Neutropenia, and Agranulocytosis [see Warnings and Precautions (5.13)]
- Hyperprolactinemia [see Warnings and Precautions (5.14)]
- Risk of Severe Neurotoxicity in Patients with Thyrotoxicosis [see Warnings and Precautions (5.15)]

6.1 Clinical Trials Experience

Because clinical trials are conducted under widely varying conditions, adverse reaction rates observed in the clinical trials of a drug cannot be directly compared to rates in the clinical trials of another drug and may not reflect the rates observed in practice.

Adverse Reactions Identified in Clinical Trials with HALDOL DECANOATE

The data described below reflect exposure to 15 mg to 500 mg (1.7 times the maximum recommended dosage) of HALDOL DECANOATE monthly in 13 clinical trials of 410 adult patients with schizophrenia or an unapproved condition. These clinical trials comprised of:

- 1 double-blind, active comparator-controlled trial with fluphenazine decanoate (Trial 1).
- 2 trials comparing HALDOL DECANOATE to oral haloperidol (Trials 2 and 3).
- 9 open-label trials.
- 1 dose-response trial.

The most common adverse reactions that occurred in ≥5% of HALDOL DECANOATE-treated patients in Trial 1 were Parkinsonism and oculogyric crisis.

Adverse reactions that occurred in ≥1% of HALDOL DECANOATE-treated patients in Trial 1 are shown in Table 2. Trial 1 was not designed to evaluate meaningful comparisons of the incidence of adverse reactions in the HALDOL DECANOATE and fluphenazine decanoate treatment groups.

Table 2: Adverse Reactions that Occurred in ≥1% of HALDOL DECANOATE-treated Patients and Fluphenazine Decanoate-treated Patients in Trial 1 [The study was not designed to evaluate meaningful comparisons of the incidence of adverse reactions in the HALDOL DECANOATE and the fluphenazine decanoate treatment groups.]
 | HALDOL DECANOATE (n=36) | Fluphenazine decanoate (n=36)
Extrapyramidal disorder:
Parkinsonism | 31% | 44%
Oculogyric crisis | 6% | 0%
Akinesia | 3% | 22%
Akathisia | 3% | 14%
Tremor | 3% | 0%
Abdominal pain | 3% | 0%
Headache | 3% | 0%

Less common adverse reactions (<1%) that occurred in Trial 1 and other adverse reactions that occurred in Trials 2 and 3, and open-label and dose-response clinical trials of HALDOL DECANOATE are listed below.

- Cardiac Disorders:Tachycardia
- Endocrine Disorders:Hyperprolactinemia
- Eye Disorders:Vision blurred
- Gastrointestinal Disorders:Constipation, Dry mouth, Salivary hypersecretion
- General Disorders and Administration Site Conditions:Weight increased, Injection site reaction
- Musculoskeletal and Connective Tissue Disorders:Muscle rigidity
- Nervous System Disorders:Dyskinesia, Dystonia, Cogwheel rigidity, Hypertonia, Masked facies, Sedation, Somnolence
- Reproductive System Disorders:Erectile dysfunction

Adverse Reactions Identified in Clinical Trials with Immediate-Release Haloperidol Products

Based on clinical trials with immediate-release haloperidol products that included 1,579 patients, the following adverse reactions were reported:

- Musculoskeletal and Connective Tissue Disorders:Torticollis, Trismus, Muscle twitching
- Nervous System Disorders:Neuroleptic malignant syndrome, Tardive dyskinesia, Bradykinesia, Hyperkinesia, Hypokinesia, Dizziness, Nystagmus
- Psychiatric Disorders:Loss of libido, Restlessness
- Reproductive System and Breast Disorders:Amenorrhea, Galactorrhea, Dysmenorrhea, Menorrhagia, Breast discomfort
- Skin and Subcutaneous Tissue Disorders:Acneiform skin reactions
- Vascular Disorders:Hypotension, Orthostatic hypotension

6.2 Postmarketing Experience

The following adverse reactions have been identified during post-approval use of haloperidol, including HALDOL DECANOATE. Because these reactions are reported voluntarily from a population of uncertain size, it is not always possible to reliably estimate their frequency or establish a causal relationship to drug exposure.

- Blood and Lymphatic System Disorders:Pancytopenia, Agranulocytosis, Thrombocytopenia, Leukopenia, Neutropenia
- Cardiac Disorders:Ventricular fibrillation, Torsade de pointes, Ventricular tachycardia, Extrasystoles, QTc interval prolongation
- Endocrine Disorders:Inappropriate antidiuretic hormone secretion
- Gastrointestinal Disorders:Vomiting, Nausea
- General Disorders and Administration Site Conditions:Sudden death, Face edema, Edema, Hyperthermia, Hypothermia, Injection site abscess, Weight decreased
- Hepatobiliary Disorders:Acute hepatic failure, Hepatitis, Cholestasis, Jaundice, Liver function test abnormal
- Immune System Disorders:Anaphylactic reaction, Hypersensitivity
- Metabolic and Nutritional Disorders:Hypoglycemia
- Musculoskeletal and Connective Tissue Disorders:Rhabdomyolysis
- Nervous System Disorders:Convulsion, Opisthotonus, Tardive dystonia
- Pregnancy, Puerperium and Perinatal Conditions:Neonatal drug withdrawal syndrome
- Psychiatric Disorders:Agitation, Confusional state, Depression, Insomnia
- Renal and Urinary Disorders:Urinary retention
- Reproductive System and Breast Disorders:Priapism, Gynecomastia
- Respiratory, Thoracic and Mediastinal Disorders:Laryngeal edema, Bronchospasm, Laryngospasm, Dyspnea
- Skin and Subcutaneous Tissue Disorders:Angioedema, Dermatitis exfoliative, Hypersensitivity vasculitis, Photosensitivity reaction, Urticaria, Pruritus, Rash, Hyperhidrosis

7 DRUG INTERACTIONS

7.1 Drugs that Prolong the QTc Interval

Avoid concomitant use of HALDOL DECANOATE with other drugs with a known potential to prolong the QTc interval. If concomitant use cannot be avoided [see Warnings and Precautions (5.2)] :

- Obtain ECGs when initiating and during concomitant use as clinically indicated.
- Obtain serum electrolytes (including potassium, calcium, phosphorus, and magnesium) when initiating and during concomitant use as clinically indicated.

QTc interval prolongation has been observed with HALDOL DECANOATE treatment. Concomitant use of HALDOL DECANOATE with other products that prolong the QTc interval may result in a greater increase in the QTc interval, and adverse reactions associated with QTc interval prolongation, including torsade de pointes, other serious arrythmias, and sudden death [see Warnings and Precautions (5.2)].

7.2 Other Clinically Significant Drug Interactions

Table 3 describes other clinically significant drug interactions of HALDOL DECANOATE.

Table 3: Other Clinically Significant Drugs Interactions [See www.fda.gov/CYPandTransporterInteractingDrugs for examples of CYP3A4 and/or CYP2D6 inhibitors, CYP3A4 inducers, and CYP2D6 substrates.]
CNS Depressants
Clinical Impact | Haloperidol may potentiate CNS depressants.
Prevention or Management | Avoid concomitant use of HALDOL DECANOATE with CNS depressants such as anesthetics, opioids, and alcohol.
CYP3A4 and/or CYP2D6 Inhibitors
Clinical Impact | CYP3A4 and/or CYP2D6 inhibitors increase haloperidol exposure (haloperidol is a CYP3A4 and CYP2D6 substrate) [see Clinical Pharmacology (12.3)]. Concomitant use of HALDOL DECANOATE and CYP3A4 and/or CYP2D6 inhibitors may increase the risk of haloperidol-associated adverse reactions.
Prevention or Management | Monitor for signs or symptoms of increased or prolonged pharmacologic effects of haloperidol. Decrease the dosage of HALDOL DECANOATE as clinically necessary.
CYP3A4 Inducers
Clinical Impact | CYP3A4 inducers decrease haloperidol exposure (haloperidol is a CYP3A4 substrate) [see Clinical Pharmacology (12.3)]. Concomitant use of HALDOL DECANOATE with CYP3A4 inducers may reduce the effectiveness of HALDOL DECANOATE.
Prevention or Management | Monitor patients and if necessary, increase the dosage of HALDOL DECANOATE.
CYP2D6 Substrates
Clinical Impact | Haloperidol is a CYP2D6 inhibitor. Plasma concentrations of CYP2D6 substrates may increase when they are concomitantly administered with HALDOL DECANOATE.
Prevention or Management | Monitor plasma concentrations of the CYP2D6 substrate, if possible. Consider reducing the dosage of the CYP2D6 substrate, if necessary. Refer to the Prescribing Information of the CYP2D6 substrate.
Dopaminergic Drugs
Clinical Impact | Haloperidol may antagonize the effects of levodopa, dopamine agonists, and other drugs intended to increase dopamine levels.
Prevention or Management | HALDOL DECANOATE is contraindicated in patients with Parkinson's disease and dementia with Lewy bodies. For conditions other than Parkinson's disease and dementia with Lewy bodies, when possible, avoid concomitant use of HALDOL DECANOATE with dopaminergic drugs [see Warnings and Precautions (5.7)] .
Anticholinergic Drugs
Clinical Impact | The healthcare provider should keep in mind the possible increase in intraocular pressure when anticholinergic drugs are administered concomitantly with HALDOL DECANOATE.
Prevention or Management | Monitor and manage patients as clinically appropriate.
Lithium
Clinical Impact | Concomitant use of HALDOL DECANOATE with lithium may cause an encephalopathic syndrome followed by irreversible brain damage [see Warnings and Precautions (5.12)] .
Prevention or Management | Monitor patients who concomitantly use HALDOL DECANOATE with lithium closely for early signs of neurological toxicity, and discontinue HALDOL DECANOATE or both HALDOL DECANOATE and lithium promptly if such signs appear.

8 USE IN SPECIFIC POPULATIONS

8.1 Pregnancy

Risk Summary

Available data from published epidemiologic studies of pregnant patients exposed to haloperidol have not established a drug-associated risk of major birth defects or miscarriage. Case reports of limb malformations in neonates have been reported in haloperidol-treated mothers; however, causal relationships were not established in these cases. There are risks to the pregnant patient from untreated schizophrenia, including increased risk of relapse, hospitalization, and suicide (see Clinical Considerations) . HALDOL DECANOATE should be used during pregnancy only if the potential benefit justifies the potential risk to the fetus.

Neonates exposed to antipsychotic drugs during the third trimester of pregnancy are at risk for extrapyramidal and/or withdrawal symptoms (agitation, hypertonia, hypotonia, tremor, somnolence, respiratory distress, and decreased feeding) following delivery (see Clinical Considerations) .

The estimated background risk of major birth defects and miscarriage in patients with schizophrenia is unknown. All pregnancies have a background risk of birth defect, loss, or other adverse outcomes. In the U.S. general population, the estimated background risk of major birth defects and miscarriage in clinically recognized pregnancies is 2–4% and 15–20%, respectively.

Clinical Considerations

Disease-associated Maternal and/or Embryo/Fetal Risk:There is risk to the pregnant patient from untreated schizophrenia, including increased risk of schizophrenia relapse, hospitalization, and suicide. Schizophrenia is associated with increased adverse perinatal outcomes, including preterm birth. It is not known if this is a direct result of the illness or other comorbid factors.

Fetal/Neonatal Adverse Reactions:Extrapyramidal and/or withdrawal symptoms, including agitation, hypertonia, hypotonia, tremor, somnolence, respiratory distress and decreased feeding have been reported in neonates who were exposed to antipsychotic drugs during the third trimester of pregnancy. Transient neonatal dyskinesia has also been reported. Some neonates recovered within hours or days without specific treatment; others required prolonged hospitalization. Monitor neonates for extrapyramidal, withdrawal, and dyskinesia symptoms and manage symptoms appropriately.

Data

Animal Data:

Rats or rabbits administered oral haloperidol at doses of 0.5 to 7.5 mg/kg (approximately 0.2 to 7 times the maximum recommended human oral dose (MRHD) of 20 mg/day based on mg/m^2body surface area) showed an increase in incidence of resorption, reduced fertility, delayed delivery, and pup mortality. No fetal abnormalities were observed at these doses in rats or rabbits. Cleft palate has been observed in mice administered oral haloperidol at a dose of 0.5 mg/kg, which is approximately 0.1 times the oral MRHD based on mg/m^2body surface area.

8.2 Lactation

Risk Summary

Literature reports suggest that haloperidol is detected in human milk of haloperidol-treated mothers with a relative infant dose ranging from 2% to 12%. Haloperidol has also been detected in the plasma and urine of breastfed infants. There has been a report of lethargy, poor feeding, and slowing of motor movements in an infant exposed to haloperidol through human milk. Haloperidol may increase prolactin levels in some patients which can lead to galactorrhea.

Monitor infants exposed to HALDOL DECANOATE via human milk for excessive sedation, irritability, poor feeding, and extrapyramidal symptoms (tremors and abnormal muscle movements).

The developmental and health benefits of breastfeeding should be considered along with the mother's clinical need for HALDOL DECANOATE and any potential adverse effects on the breastfed child from HALDOL DECANOATE or from the mother's underlying condition.

8.3 Females and Males of Reproductive Potential

Infertility

Females:Based on the pharmacologic action of haloperidol (D2 receptor antagonism), treatment with HALDOL DECANOATE may result in an increase in serum prolactin levels, which may lead to a reduction in fertility in females of reproductive potential.

Males:Based on animal studies, male fertility may be impaired by treatment with haloperidol [see Nonclinical Toxicology (13.1)] .

8.4 Pediatric Use

Safety and effectiveness of HALDOL DECANOATE have not been established in pediatric patients.

8.5 Geriatric Use

Clinical studies of HALDOL DECANOATE did not include sufficient numbers of patients 65 years of age and older to determine whether they respond differently from younger adult patients.

The exposure of haloperidol may be higher in geriatric patients compared to young adult patients. Results from small clinical studies suggest a lower clearance and a longer elimination half-life of haloperidol in geriatric patients [see Clinical Pharmacology (12.3)]. Consider starting at the low end of the recommended dosing range for the first HALDOL DECANOATE dose in geriatric patients [see Dosage and Administration (2.1)] .

Antipsychotic drugs increase the risk of death in elderly patients with dementia-related psychosis. HALDOL DECANOATE is not approved for the treatment of patients with dementia-related psychosis [see Warnings and Precautions (5.1)] .

Elderly patients with dementia-related psychosis treated with antipsychotics had an increased risk of cerebrovascular adverse reactions (e.g., stroke, transient ischemic attack) including fatalities, compared to those treated with placebo [see Warnings and Precautions (5.4)] .

Antipsychotic drugs increase the risk of tardive dyskinesia and this risk appears to be highest among the elderly, particularly elderly women [see Warnings and Precautions (5.5)] .

8.6 Hepatic Impairment

Haloperidol is extensively metabolized in the liver, therefore, haloperidol concentrations may be higher in patients with hepatic impairment compared to patients with normal hepatic function. In patients with hepatic impairment, consider starting at the low end of the recommended dosing range for the first HALDOL DECANOATE dose [see Dosage and Administration (2.1)].

10 OVERDOSAGE

Reported overdose signs and symptoms are those resulting from an exaggeration of the drug's known pharmacologic effects (e.g., drowsiness and sedation, tachycardia and hypotension) and adverse reactions, the most prominent of which would be: 1) severe extrapyramidal symptoms, 2) hypotension, or 3) sedation. Patients may appear comatose with respiratory depression and hypotension which could be severe enough to produce a shock-like state. Extrapyramidal reactions may be manifested by muscular weakness or rigidity and a generalized or localized tremor, as demonstrated by the akinetic or agitans types, respectively. The risk of QTc interval prolongation and torsade de pointes should be considered [see Adverse Reactions (6.2)] .

Management of Overdose

There is no specific antidote for a haloperidol overdose.

- Should hypotension occur and a vasopressor be required, epinephrine must not be used since HALDOL DECANOATE may block its vasopressor activity, and paradoxical further lowering of the blood pressure may occur. Instead, metaraminol, phenylephrine or norepinephrine should be used.
- In case of severe extrapyramidal reactions, antiparkinson drugs should be administered, and should be continued for several weeks, and then withdrawn gradually as extrapyramidal symptoms may emerge if discontinued abruptly.
- Monitor ECG and vital signs for signs of QTc interval prolongation or dysrhythmias and continue monitoring until the dysrhythmias resolve and the haloperidol-induced QTc interval prolongation resolves.
- Dialysis is not recommended in the treatment of overdose because it removes only very small amounts of haloperidol.

Consider contacting the Poison Help line (1-800-222-1222) or a medical toxicologist for additional overdose management recommendations.

11 DESCRIPTION

HALDOL DECANOATE (haloperidol decanoate injection) is the decanoate ester of haloperidol, for intramuscular use. Haloperidol is a typical antipsychotic. The structural formula of haloperidol decanoate is 4-(4-chlorophenyl)-1-[4-(4-fluorophenyl)-4-oxobutyl] piperidin-4-yl decanoate:

The molecular formula is C31H41CIFNO3and has a molecular weight of 530.12. Haloperidol decanoate is almost insoluble in water (0.01 mg/mL) but is soluble in most organic solvents.

Each mL of HALDOL DECANOATE contains:

- 50 mg of haloperidol (present as 70.5 mg of haloperidol decanoate) in a sesame oil vehicle (0.85 g/mL), with 15 mg/mL benzyl alcohol as a preservative.
- 100 mg of haloperidol (present as 141 mg of haloperidol decanoate) in a sesame oil vehicle (0.85 g/mL), with 15 mg/mL benzyl alcohol as a preservative.

12 CLINICAL PHARMACOLOGY

12.1 Mechanism of Action

The mechanism of action of HALDOL DECANOATE for the treatment of schizophrenia in adults is unclear. However, its effect in schizophrenia could be mediated through its activity as an antagonist at central dopamine type 2 receptors. Haloperidol also binds to alpha-1 adrenergic receptors, but with lower affinity, and displays minimal binding to muscarinic cholinergic and histaminergic (H1) receptors.

12.2 Pharmacodynamics

The exposure-response relationship and time course of pharmacodynamic response for the safety and effectiveness of haloperidol have not been fully characterized.

12.3 Pharmacokinetics

Absorption

The plasma concentrations of haloperidol gradually rise, reaching a peak at about 6 days after the HALDOL DECANOATE injection, and fall thereafter, with an apparent half-life of about 3 weeks. Steady state plasma concentrations of haloperidol are achieved within 2 to 4 months in patients receiving monthly HALDOL DECANOATE injections. The relationship between the HALDOL DECANOATE dosage and plasma haloperidol concentration is roughly linear for dosages below 450 mg (1.5 times the maximum recommended dosage [see Dosage and Administration (2.1)] ; however, the pharmacokinetics of haloperidol following intramuscular injections can be quite variable between patients.

Elimination

Metabolism:Haloperidol is metabolized by several routes. The major pathways are glucuronidation and ketone reduction. The cytochrome P450 enzyme system is also involved, particularly CYP3A4 and, to a lesser extent, CYP2D6.

Excretion:

Less than 3% of administered haloperidol is eliminated unchanged in the urine. The apparent half-life of haloperidol following intramuscular injection of HALDOL DECANOATE is about 3 weeks.

Specific Populations

Patients with Hepatic Impairment

Studies in patients with hepatic impairment have not been conducted. Haloperidol is extensively metabolized in the liver, therefore, haloperidol concentrations may be higher in patients with hepatic impairment compared to patients with normal hepatic function [see Use in Specific Populations (8.6)].

Geriatric Patients

Haloperidol plasma concentrations in geriatric patients were higher than in younger adult patients when administered the same dosage. Results from small clinical studies suggest a lower clearance and a longer elimination half-life of haloperidol in geriatric patients. The results are within the observed variability in haloperidol pharmacokinetics [see Use in Specific Populations (8.5)] .

Patients with Renal Impairment

Studies in patients with renal impairment have not been conducted.

Drug Interaction Studies

Ketoconazole and Paroxetine

The haloperidol plasma concentrations increased when ketoconazole (400 mg/day, strong CYP3A4 inhibitor) and paroxetine (20 mg/day, strong CYP2D6 inhibitor) were concomitantly administered with haloperidol [see Drug Interactions (7.2)] .

Valproate:Sodium valproate, a drug known to inhibit glucuronidation, does not affect haloperidol plasma concentrations.

Rifampin:In a study with 12 patients with schizophrenia, concomitant administration of oral haloperidol and rifampin, a strong CYP3A4 inducer, resulted in decreased plasma haloperidol concentrations by a mean of 70% and increased mean scores on the Brief Psychiatric Rating Scale from baseline. In five other patients with schizophrenia treated with oral haloperidol and rifampin, discontinuation of rifampin resulted in a mean 3.3-fold increase in haloperidol concentrations [see Drug Interactions (7.2)] .

Carbamazepine:In a study with 11 patients with schizophrenia, concomitant administration of haloperidol and increasing doses of carbamazepine, a CYP3A4 strong inducer, resulted in decreased haloperidol plasma concentrations in a linear manner with increasing carbamazepine concentrations [see Drug Interactions (7.2)].

Effect of Haloperidol on Other Drugs

Haloperidol is an inhibitor of CYP2D6. Plasma concentrations of CYP2D6 substrates may increase when they are concomitantly administered with haloperidol [see Drug Interactions (7.2)] .

13 NONCLINICAL TOXICOLOGY

13.1 Carcinogenesis, Mutagenesis, and Impairment of Fertility

Carcinogenesis

Carcinogenicity studies using oral haloperidol were conducted in Wistar rats (dosed at up to 5 mg/kg daily for 24 months) and in Albino Swiss mice (dosed at up to 5 mg/kg daily for 18 months).

- In the rat study, survival was reduced in all haloperidol dose groups, decreasing the number of rats at risk for developing tumors. However, a relatively greater number of rats survived to the end of the study in the high dose haloperidol male and female groups. These haloperidol-treated rats at doses up to approximately 2.5 times the maximum recommended human oral dose (MRHD) of haloperidol of 20 mg/day based on mg/m^2body surface area did not have a greater incidence of tumors than control-treated rats.
- In female mice, there was a statistically significant increase in mammary gland neoplasia and total tumor incidence at haloperidol doses approximately 0.3 and 1.2 times the oral MRHD based on mg/m^2body surface area and there was statistically significant increase in pituitary gland neoplasia at approximately 1.2 times the oral MRHD. In male mice, no statistically significant differences in incidences of total tumors or specific tumor types were noted.

Tissue culture experiments indicate that approximately one-third of human breast cancers are prolactin dependent in vitro, a factor of potential importance if the prescription of these drugs is contemplated in a patient with a previously detected breast cancer. An increase in mammary neoplasms has been found in rodents after chronic administration of antipsychotic drugs [see Warnings and Precautions (5.14)] .

Mutagenesis

No mutagenic potential of haloperidol decanoate was found in the Ames Salmonella assay. Negative or inconsistent positive findings have been obtained in in vitroand in vivostudies of effects of haloperidol on chromosome structure and number. The available cytogenetic evidence is considered too inconsistent to be conclusive.

Impairment of Fertility

Haloperidol was orally administered to male rats at doses of 0.5, 2.5, and 15 mg/kg/day (approximately 0.2 to 7 times the oral MRHD based on mg/m^2body surface area) for 63 days prior to mating with untreated females. Decreases in mating performance and fertility, as well as markedly decreased motor activity, was observed at seven times the oral MRHD based on mg/m^2body surface area. The NOAEL of 2.5 mg/kg/day is approximately equal to the oral MRHD based on mg/m^2body surface area.

16 HOW SUPPLIED/STORAGE AND HANDLING

How Supplied

HALDOL DECANOATE (haloperidol decanoate injection) is a clear, yellow to light amber viscous liquid, free from visible foreign material and available as:

- haloperidol 50 mg/mL (present as haloperidol decanoate)
  - NDC 50458-253-03, 3 × 1 mL single-dose ampules, packaged in a carton
- haloperidol 100 mg/mL (present as haloperidol decanoate)
  - NDC 50458-254-14, 5 × 1 mL single-dose ampules, packaged in a carton

Storage and Handling

Store at room temperature 20°C to 25°C (68°F to 77°F) with excursions permitted between 15°C and 30°C (59°F and 86°F). Do not refrigerate or freeze. Protect from light. Discard unused portion.

17 PATIENT COUNSELING INFORMATION

Sudden Death, Torsades de Pointes, and QTc Interval Prolongation

Inform patients that there have been reports of sudden death, torsades de Pointes, and QTc interval prolongation in haloperidol-treated patients. Advise patients or caregivers to seek immediate medical attention if they suspect or develop signs or symptoms associated with the clinical consequences of QTc interval prolongation [see Warnings and Precautions (5.2)] .

Tardive Dyskinesia

Inform patients that tardive dyskinesia (TD) may develop with HALDOL DECANOATE. Counsel patients on the signs and symptoms of tardive dyskinesia and to contact their healthcare provider if these abnormal movements occur [see Warnings and Precautions (5.5)] .

Neuroleptic Malignant Syndrome

Counsel patients about a potentially fatal adverse reaction, Neuroleptic Malignant Syndrome (NMS), that has been reported with administration of antipsychotic drugs. Advise patients, family members, or caregivers to contact the health care provider or to report to the emergency room if they experience signs and symptoms of NMS [see Warnings and Precautions (5.6)] .

Hypersensitivity Reactions

Inform patients of the potential risk of hypersensitivity reactions. Advise patients to stop taking HALDOL DECANOATE and seek immediate attention if signs or symptoms of a hypersensitivity reaction occur [see Warnings and Precautions (5.9)] .

Falls

Inform patients that HALDOL DECANOATE can cause somnolence, orthostatic hypotension, motor instability and sensory abnormality that may lead to falls. Advise patients to notify their healthcare provider if any of these symptoms occur [see Warnings and Precautions (5.10)].

Potential for Cognitive and Motor Impairment

Inform patients of the risk and advise them to not drive a motor vehicle or operate hazardous machinery until they are reasonably certain that treatment with HALDOL DECANOATE does not impair their cognitive and motor functions [see Warnings and Precautions (5.11)].

Leukopenia/Neutropenia

Advise patients with a pre-existing low WBC or a history of drug induced leukopenia or neutropenia that they should have their CBC monitored while taking HALDOL DECANOATE [see Warnings and Precautions (5.13)] .

Hyperprolactinemia

Counsel patients on signs and symptoms of hyperprolactinemia that may be associated with chronic use of HALDOL DECANOATE. Advise the patients to seek medical attention if they experience any of the following: amenorrhea, galactorrhea, erectile dysfunction or gynecomastia [see Warnings and Precautions (5.14)].

Pregnancy

Advise pregnant patients to notify their health care provider if they become pregnant or intend to become pregnant during treatment with HALDOL DECANOATE. Advise patients that HALDOL DECANOATE exposure during the third trimester of pregnancy may cause adverse effects in the neonate, including agitation, hypertonia, hypotonia, tremor, somnolence, respiratory distress, and decreased feeding [see Use in Specific Populations (8.1)] .

Lactation

Advise breastfeeding patients using HALDOL DECANOATE to monitor infants for excess sedation, irritability, poor feeding, and extrapyramidal symptoms (tremors and abnormal muscle movements) and to seek medical care if they notice these signs [see Use in Specific Populations (8.2)] .

Infertility

Advise females and males of reproductive potential that HALDOL DECANOATE may impair fertility due to an increase in serum prolactin levels [see Use in Specific Populations (8.3)] .

Drug Interactions

Advise patients to inform their health care provider before starting or discontinuing a prescription drug, nonprescription drug, or supplement [see Warnings and Precautions (5.2)and Drug Interactions (7)] .

Product of Belgium

Manufactured for:
Janssen Pharmaceuticals, Inc.
Titusville, NJ 08560, USA

For patent information: www.janssenpatents.com

© Johnson & Johnson and its affiliates 2025

PRINCIPAL DISPLAY PANEL - 50 mg/mL box

NDC 50458-253-03

IM Use
Only

Haldol®
(HALOPERIDOL)
Decanoate 50

50
INJECTION
50 mg/mL*

3 x 1-mL AMPULS Sterile

*Each mL contains 50 mg haloperidol
as 70.5 mg haloperidol decanoate in
a sesame oil vehicle, with 1.2% (w/v)
benzyl alcohol as a preservative.

Store at controlled room temperature
(15°-30°C, 59°-86°F).
Do not refrigerate or freeze.

Rx only.

For Intramuscular Use Only.

PROTECT FROM LIGHT.

For dosage and other prescribing
information, see accompanying
product literature.

The dose of HALDOL Decanoate 50
should be expressed in terms of its
haloperidol content.

Dispense in a light-resistant
container as defined in the official
compendium.

Keep out of reach of children.

Janssen

PRINCIPAL DISPLAY PANEL - 100 mg/mL Box

NDC 50458-254-14

IM Use
Only

Haldol®
(HALOPERIDOL)
Decanoate 100

100
INJECTION
100 mg/mL*

5 x 1-mL AMPULS Sterile

*Each mL contains 100 mg haloperidol
as 141 mg haloperidol decanoate in a
sesame oil vehicle, with 1.2% (w/v)
benzyl alcohol as a preservative.

Store at controlled room temperature
(15°-30°C, 59°-86°F).
Do not refrigerate or freeze.

Rx only.

For Intramuscular Use Only.

PROTECT FROM LIGHT.

For dosage and other prescribing
information, see accompanying
product literature.

The dose of HALDOL Decanoate 100
should be expressed in terms of its
haloperidol content.

Dispense in a light-resistant
container as defined in the official
compendium.

Keep out of reach of children.

Janssen